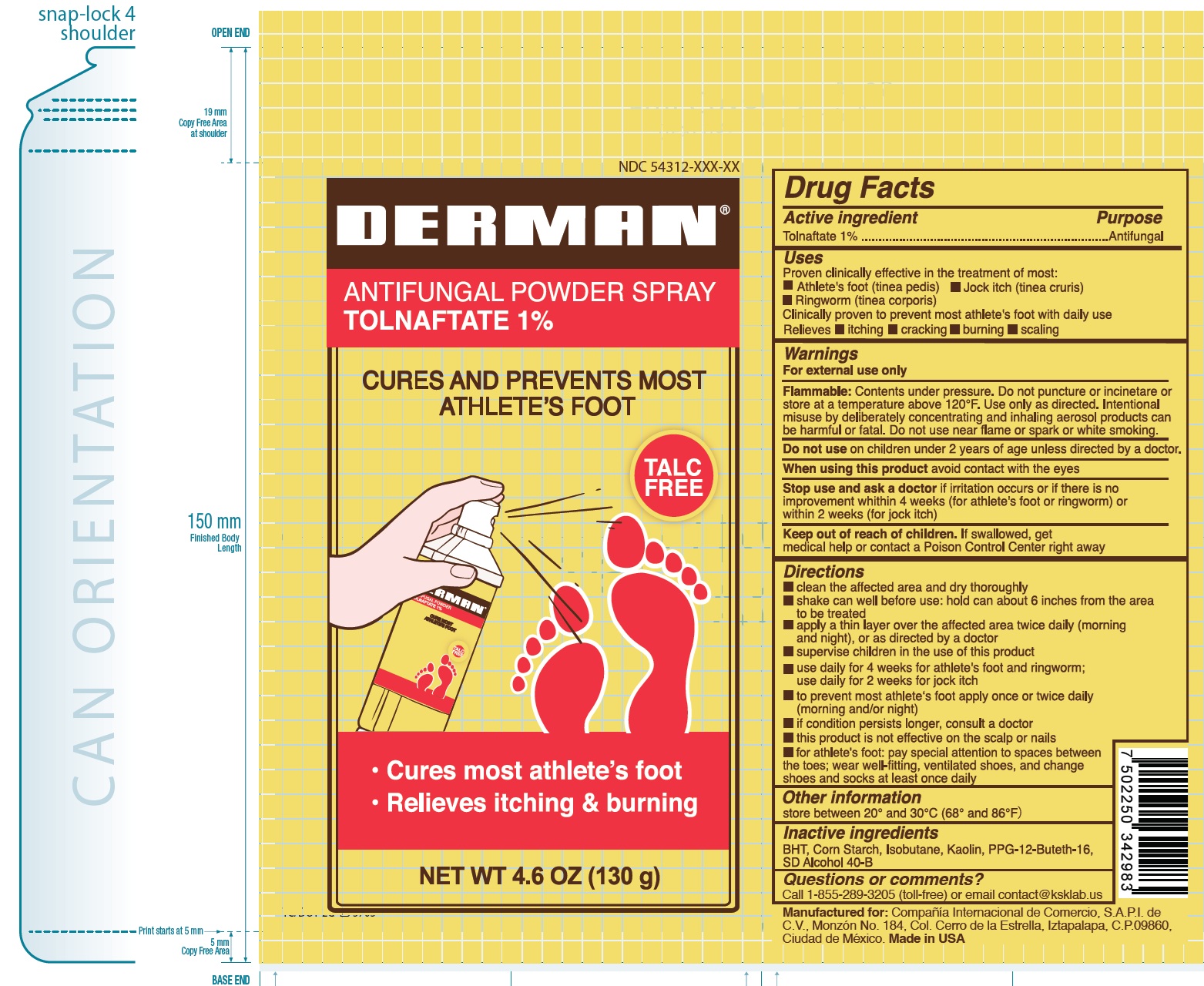 DRUG LABEL: Derman Antifungal
NDC: 54312-230 | Form: AEROSOL, POWDER
Manufacturer: Compania Internacional de Comercio, S.A.P.I. de C.V.
Category: otc | Type: HUMAN OTC DRUG LABEL
Date: 20260106

ACTIVE INGREDIENTS: TOLNAFTATE 10 mg/1 g
INACTIVE INGREDIENTS: ALCOHOL; BUTYLATED HYDROXYTOLUENE; STARCH, CORN; ISOBUTANE; KAOLIN; PPG-12-BUTETH-16

Derman Antifungal Powder Spray

Active ingredient

Tolnaftate 1%

Purpose

Antifungal

Uses

Proven clinically effective in the treatment of most:

• Athlete's foot (tinea pedis) • Jock itch (tinea cruris) • Ringworm (tinea corporis)
Clinically proven to prevent most athlete's foot with daily use Relieves • itching • cracking • burning • scaling

Warnings

For external use only

Flammable: Contents under pressure. Do not puncture or incinetare or store at a temperature above 120°F. Use only as directed. Intentional misuse by deliberately concentrating and inhaling aerosol products can be harmful or fatal. Do not use near flame or spark or white smoking.

Do not use

on children under 2 years of age unless directed by a doctor.

When using this product

avoid contact with the eyes

Stop use and ask a doctor

if irritation occurs or if there is no improvement whithin 4 weeks (for athlete's foot or ringworm) or within 2 weeks (for jock itch)

Keep out of reach of children.

If swallowed, get medical help or contact a Poison Control Center right away

Directions

• clean the affected area and dry thoroughly
• shake can well before use: hold can about 6 inches from the area to be treated
• apply a thin layer over the affected area twice daily (morning and night), or as directed by a doctor
• supervise children in the use of this product
• use daily for 4 weeks for athlete's foot and ringworm; use daily for 2 weeks for jock itch
• to prevent most athlete's foot apply once or twice daily (morning and/or night)
• if condition persists longer, consult a doctor
• this product is not effective on the scalp or nails
• for athlete's foot: pay special attention to spaces between the toes; wear well-fitting, ventilated shoes, and change shoes and socks at least once daily

Other information

store between 20° and 30°C (68° and 86°F)

Inactive ingredients

BHT, Corn Starch, Isobutane, Kaolin, PPG-12-Buteth-16, SD Alcohol 40-B

Questions or comments?

Call 1-855-289-3205 (toll-free) or email contact@ksklab.us